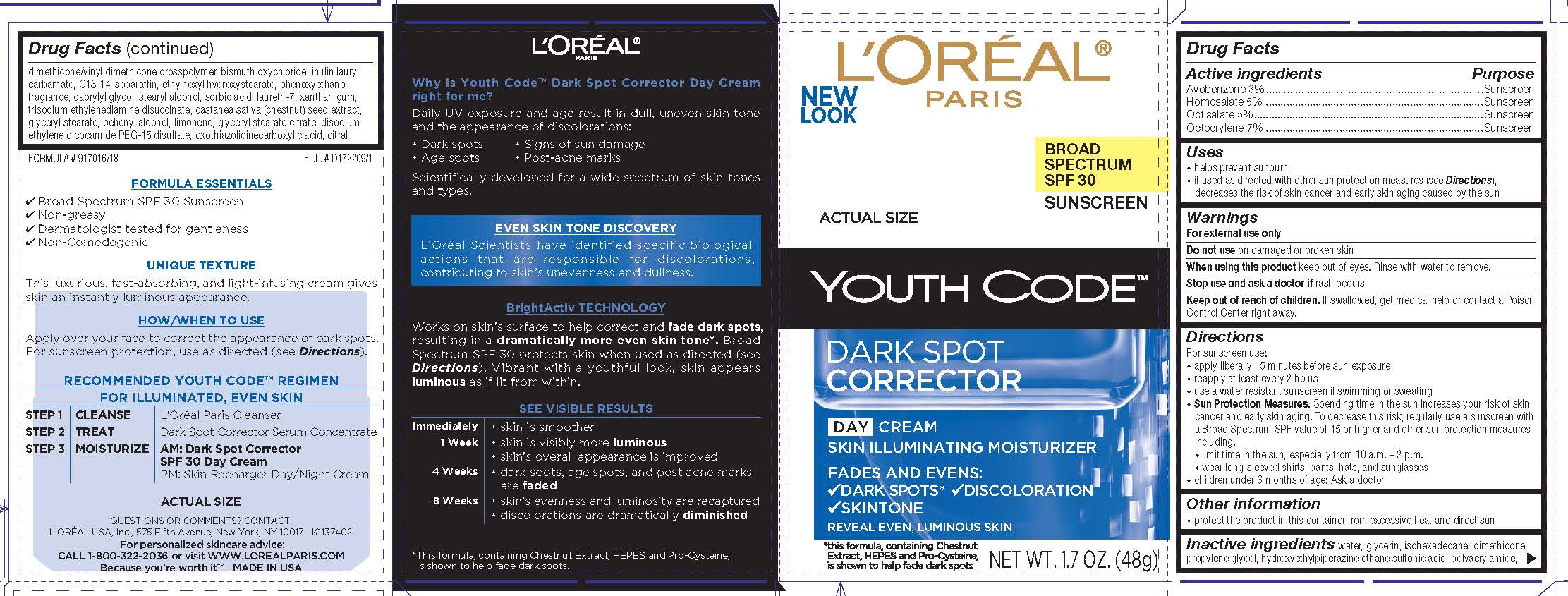 DRUG LABEL: LOreal Paris Youth Code Dark Spot Corrector Broad Spectrum SPF 30 Sunscreen
NDC: 49967-207 | Form: CREAM
Manufacturer: L'Oreal USA Products Inc
Category: otc | Type: HUMAN OTC DRUG LABEL
Date: 20231229

ACTIVE INGREDIENTS: Avobenzone 30 mg/1 g; Homosalate 50 mg/1 g; Octisalate 50 mg/1 g; Octocrylene 70 mg/1 g
INACTIVE INGREDIENTS: WATER; GLYCERIN; ISOHEXADECANE; DIMETHICONE; PROPYLENE GLYCOL; HYDROXYETHYLPIPERAZINE ETHANE SULFONIC ACID; POLYACRYLAMIDE (10000 MW); DIMETHICONE/VINYL DIMETHICONE CROSSPOLYMER (HARD PARTICLE); BISMUTH OXYCHLORIDE; C13-14 ISOPARAFFIN; ETHYLHEXYL HYDROXYSTEARATE; PHENOXYETHANOL; CAPRYLYL GLYCOL; STEARYL ALCOHOL; SORBIC ACID; LAURETH-7; XANTHAN GUM; TRISODIUM ETHYLENEDIAMINE DISUCCINATE; SPANISH CHESTNUT; GLYCERYL MONOSTEARATE; DOCOSANOL; LIMONENE, (+)-; GLYCERYL STEARATE CITRATE; DISODIUM ETHYLENE DICOCAMIDE PEG-15 DISULFATE; OXOTHIAZOLIDINECARBOXYLIC ACID; CITRAL

Drug Facts

Active ingredients

Avobenzone 3%

Homosalate 5%

Octisalate 5%

Octocrylene 7%

Purpose

Sunscreen

Uses

- helps prevent sunburn
- if used as directed with other sun protection measures (see Directions), decreases the risk of skin cancer and early skin aging caused by the sun

Warnings

For external use only

Do not use

on damaged or broken skin

When using this product

keep out of eyes. Rinse with water to remove.

Stop use and ask a doctor if

rash occurs

Keep out of reach of children.

If swallowed, get medical help or contact a Poison Control Center right away.

Directions

For sunscreen use:
● apply liberally 15 minutes before sun exposure
● reapply at least every 2 hours
● use a water resistant sunscreen if swimming or sweating
● Sun Protection Measures. Spending time in the sun increases your risk of skin cancer and early skin aging. To decrease this risk, regularly use a sunscreen with a Broad Spectrum SPF value of 15 or higher and other sun protection measures including:
● limit time in the sun, especially from 10 a.m. – 2 p.m.
● wear long-sleeved shirts, pants, hats, and sunglasses
● children under 6 months of age: Ask a doctor

Other information

protect the product in this container from excessive heat and direct sun

Inactive ingredients

water, glycerin, isohexadecane, dimethicone, propylene glycol, hydroxyethylpiperazine ethane sulfonic acid, polyacrylamide, dimethicone/vinyl dimethicone crosspolymer, bismuth oxychloride, inulin lauryl carbamate, c13-14 isoparaffin, ethylhexyl hydroxystearate, phenoxyethanol, fragrance, caprylyl glycol, stearyl alcohol, sorbic acid, laureth-7, xanthan gum, trisodium ethylenediamine disuccinate, castanea sativa (chestnut) seed extract, glyceryl stearate, behenyl alcohol, limonene, glyceryl stearate citrate, disodium ethylene dicocamide PEG-15 disulfate, oxothiazolidinecarboxylic acid, citral